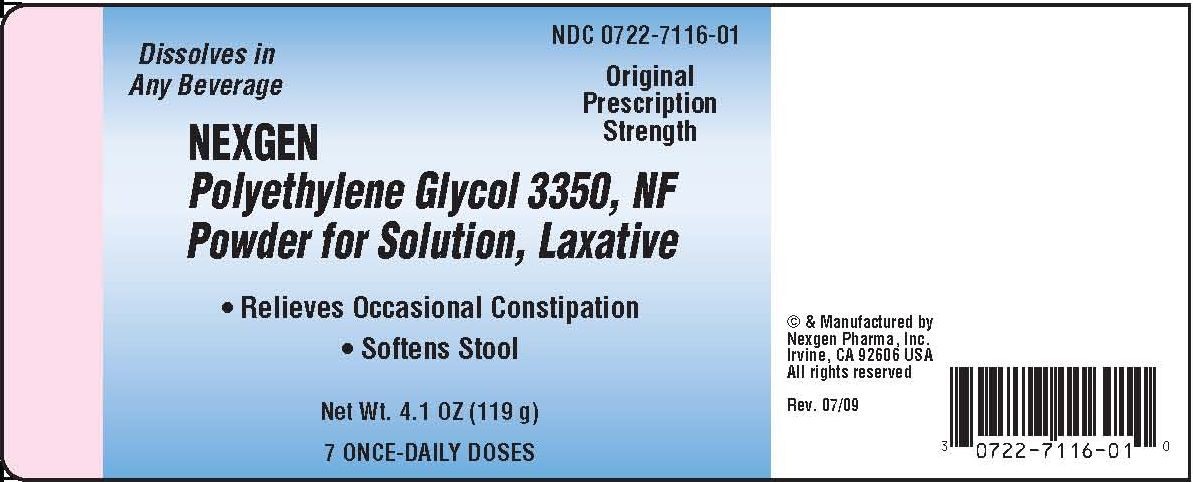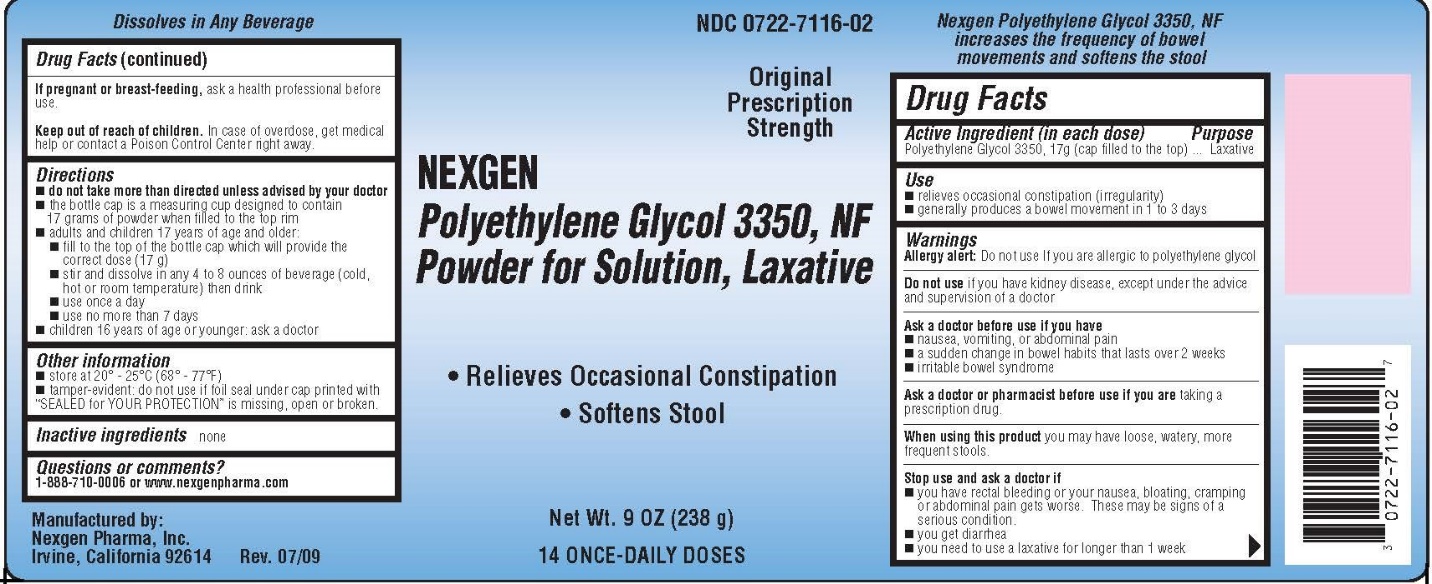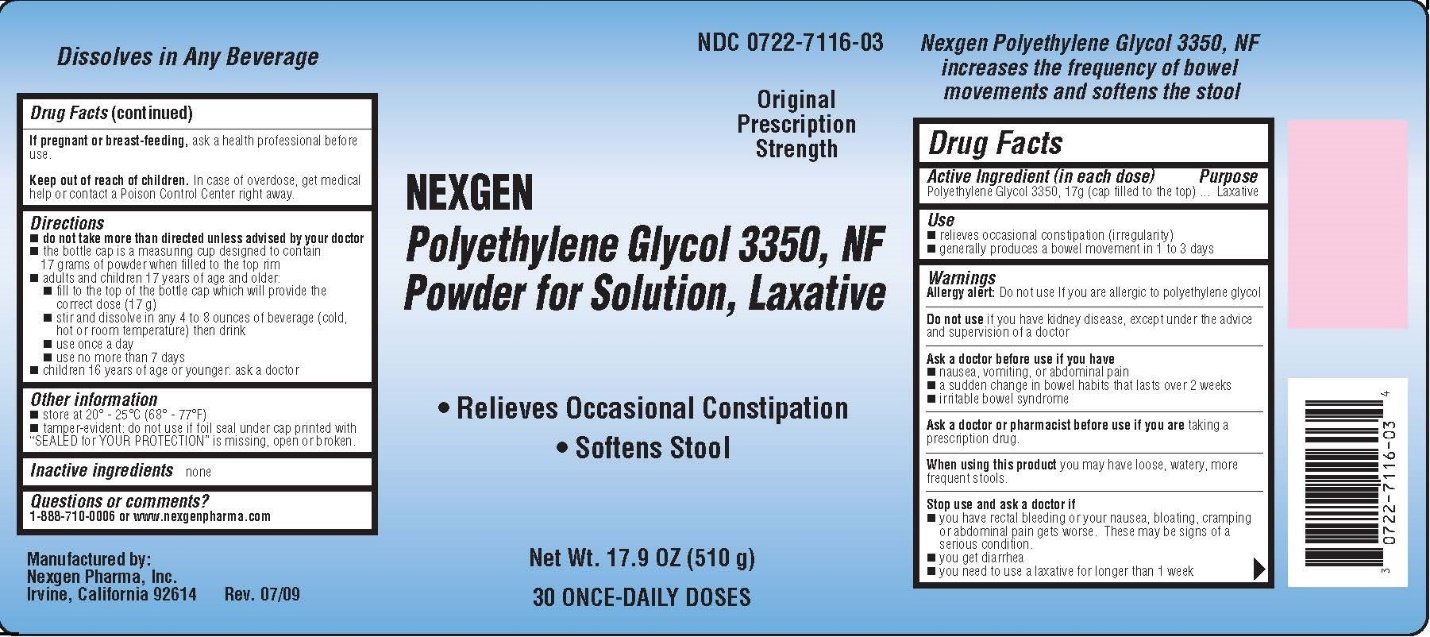 DRUG LABEL: Polyethylene Glycol 3350, NF Powder for Solution, Laxative
NDC: 0722-7116 | Form: POWDER, FOR SOLUTION
Manufacturer: Nexgen Pharma, Inc.
Category: otc | Type: HUMAN OTC DRUG LABEL
Date: 20190904

ACTIVE INGREDIENTS: POLYETHYLENE GLYCOL 3350 17 g/1 d

Drug Facts

Active ingredient (in each dose)

Polyethylene Glycol 3350, 17 grams (cap filled to the top)

Purpose

Osmotic Laxative

Keep Out of Reach of Children

In case of overdose, get medical help or contact a Poison Control Center right away.

Uses

- Relieves occasional constipation (irregularity).
- Generally, produces a bowel movement in 1 to 3 days.

Warnings

Allergy alert: Do not use If you are allergic to polyethylene glycol.

Do not use if you have kidney disease, except under the advice and supervision of a doctor.

Ask a doctor before use if you have:

- nausea, vomiting or abdominal pain.
- a sudden change in bowel habits that lasts over 2 weeks.
- irritable bowel syndrome.

Ask a doctor or pharmacist before use if you are taking a prescription drug.

When using this product, you may have loose, watery, more frequent stools.

Stop use and ask a doctor if:

- you have rectal bleeding, or your nausea, bloating, cramping or abdominal pain gets worse. These may be signs of a serious condition.
- you get diarrhea.
- you need to use a laxative for longer than 1 week.

If pregnant or breast-feeding, ask a health professional before use.

Directions

- Do not take more than directed unless advised by your doctor.
- The bottle cap is a measuring cup designed to contain 17 grams of powder when filled to the top rim.
- Adults and children 17 years of age and older:
  - Fill to the top of the bottle cap which will provide the correct dose (17 g).
  - Stir and dissolve in any 4 to 8 ounces of beverage (cold, hot, or room temperature), then drink.
  - Ensure that the powder is fully dissolved before drinking.
  - Do not drink if there are any clumps.
  - Use once a day.
  - Use no more than 7 days.

Children 16 years of age or younger, ask a doctor.

Other Information

- Store at 20°C – 25°C (68°F – 77°F).
- Tamper-evident: Do not use if foil seal under cap, printed with “SEALED FOR YOUR PROTECTION” is missing, open, or broken.

Inactive ingredients

None.

Questions or Comments?

For serious adverse events call Nexgen Pharma, Inc. at 1-888-710-0006 or contact online at www.nexgenpharma.com.

Manufactured by: Nexgen Pharma, Inc., Irvine, CA 92606, USA

Rev. 09/2019

Label Principal Display Panel

17.9 oz Container Label

Label Principal Display Panel

9 oz Container Label

Label Principal Display Panel

4.1 oz Container Label - Drug Facts on Extended Content Label